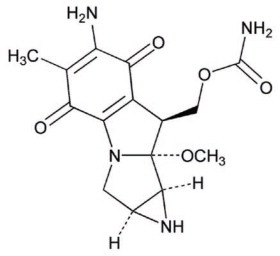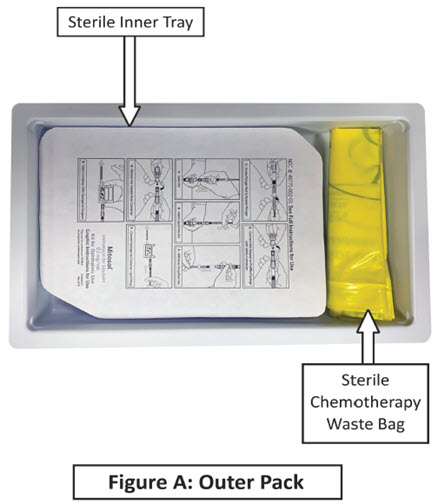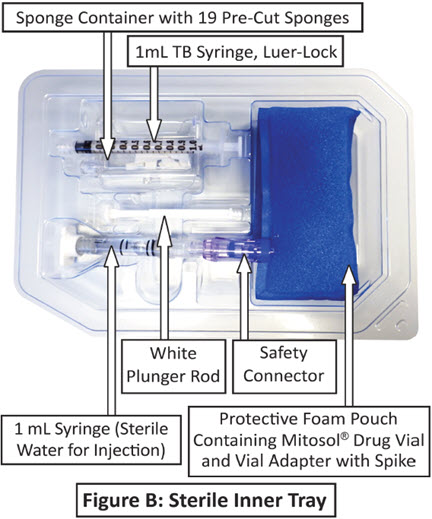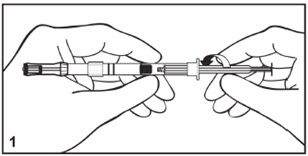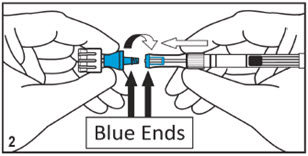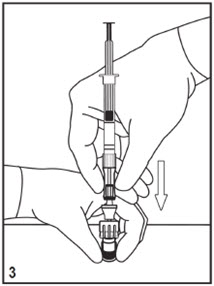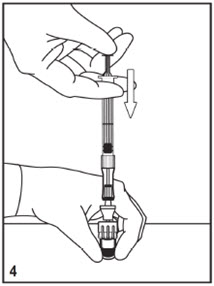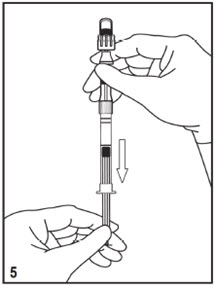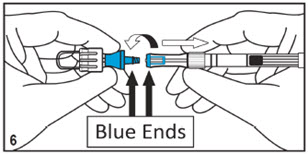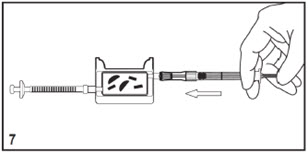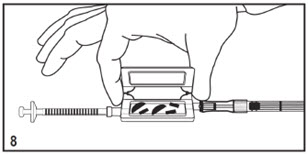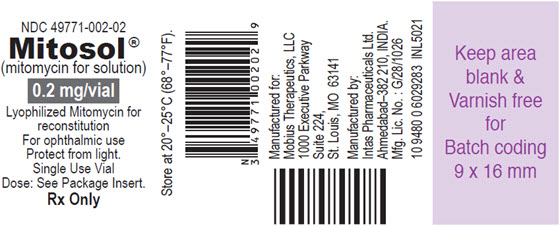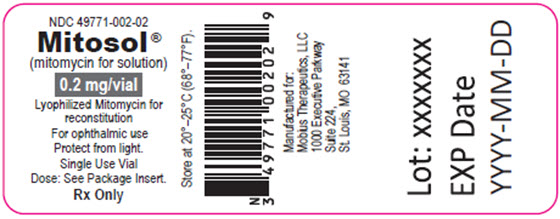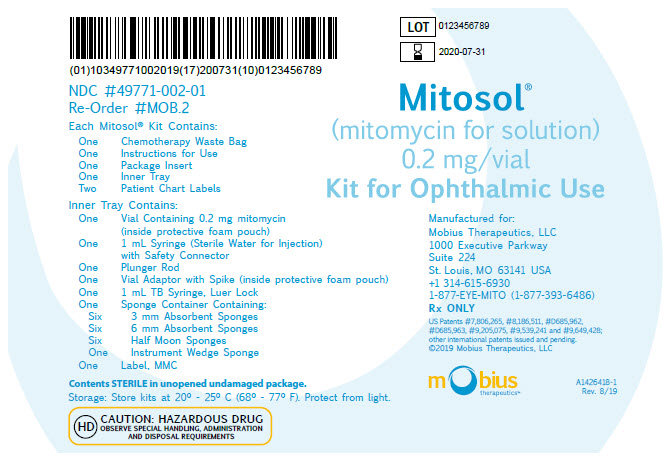 DRUG LABEL: Mitosol
NDC: 49771-002 | Form: KIT | Route: OPHTHALMIC
Manufacturer: Mobius Therapeutics LLC
Category: prescription | Type: HUMAN PRESCRIPTION DRUG LABEL
Date: 20250423

ACTIVE INGREDIENTS: Mitomycin 0.2 mg/1 mL
INACTIVE INGREDIENTS: mannitol; water

HIGHLIGHTS OF PRESCRIBING INFORMATION

These highlights do not include all the information needed to use MITOSOL® safely and effectively. See full prescribing information for MITOSOL®.
MITOSOL® (mitomycin for solution) for ophthalmic use
Initial U.S. Approval: 1974

1 INDICATIONS AND USAGE

Mitosol® is an antimetabolite indicated as an adjunct to ab externo glaucoma surgery. (1)

2 DOSAGE AND ADMINISTRATION

Mitosol® is intended for topical application to the surgical site of glaucoma filtration surgery. It is not intended for intraocular administration. (2)

- Each vial of Mitosol® contains 0.2 mg of mitomycin and mannitol in a 1:2 concentration ratio. To reconstitute, add 1 mL of Sterile Water for Injection, then shake to dissolve. If product does not dissolve immediately, allow to stand at room temperature until the product has dissolved into solution. (2.2)
- Fully saturate sponges provided within the Mitosol® Kit utilizing the entire reconstituted contents of the vial in the manner prescribed in the Instructions for Use. (2.3)
- Apply fully saturated sponges equally to the treatment area, in a single layer, with the use of a surgical forceps. Keep the sponges on the treatment area for two (2) minutes, then remove and return to the Mitosol® Tray for defined disposal. (2.3)

3 DOSAGE FORMS AND STRENGTHS

Each vial contains a sterile lyophilized mixture of 0.2 mg mitomycin and 0.4 mg mannitol; when reconstituted with Sterile Water for Injection, the solution contains 0.2 mg/mL mitomycin. (3)

4 CONTRAINDICATIONS

- Hypersensitivity to mitomycin. (4.1)

5 WARNINGS AND PRECAUTIONS

- Cell Death: Mitomycin is cytotoxic. Use of mitomycin in concentrations higher than 0.2 mg/mL or use for longer than 2 minutes may lead to unintended corneal and/or scleral damage including thinning or perforation. Direct contact with the corneal endothelium will result in cell death. (5.1)
- Hypotony: The use of mitomycin has been associated with an increased incidence of post-operative hypotony. (5.2)
- Cataract Development: Use in phakic patients has been correlated to a higher incidence of lenticular change and cataract formation. (5.3)
- Embryo-Fetal Toxicity: Can cause fetal harm. Advise of potential risk to a fetus. Verify pregnancy status in females of reproductive potential prior to use. (5.4, 8.1, 8.3)

6 ADVERSE REACTIONS

The most frequent adverse reactions to Mitosol® occur locally and include hypotony, hypotony maculopathy, blebitis, endophthalmitis, vascular reactions, corneal reactions, and cataract. (6.1)

To report SUSPECTED ADVERSE REACTIONS, contact Mobius Therapeutics LLC at 1-877-393-6486 or FDA at 1-800-FDA-1088 or www.fda.gov/medwatch

FULL PRESCRIBING INFORMATION

1 INDICATIONS AND USAGE

Mitosol® is an antimetabolite indicated for use as an adjunct to ab externo glaucoma surgery.

2 DOSAGE AND ADMINISTRATION

2.1 Important Administration Instructions

Mitosol® is intended for topical application to the surgical site of glaucoma filtration surgery. Mitosol® is a cytotoxic drug. It is not intended for intraocular administration. If intraocular administration occurs, cell death leading to corneal infarction, retinal infarction, and ciliary body atrophy may result. Verify pregnancy status in females of reproductive potential prior to using Mitosol®.

2.2 Method of Reconstitution

Each vial of Mitosol® contains 0.2 mg of mitomycin and mannitol in a 1:2 concentration ratio. To reconstitute, add 1 mL of Sterile Water for Injection, then shake to dissolve. If product does not dissolve immediately, allow to stand at room temperature until the product dissolves into solution.

2.3 Method of Use

Sponges provided within the Mitosol® Kit should be fully saturated with the entire reconstituted contents in the manner prescribed in the Instructions for Use. A treatment area approximating 10mm x 6mm +/- 2mm should be treated with the Mitosol®. Apply fully saturated sponges equally to the treatment area, in a single layer, with the use of a surgical forceps. Keep the sponges on the treatment area for two (2) minutes, then remove and return to the Mitosol® Tray for defined disposal in the Chemotherapy Waste Bag provided.

2.4 Stability

Lyophilized Mitosol® stored at 20°C to 25°C (68°F to 77°F) is stable for the shelf life indicated on the package. Avoid excessive heat. Protect from light.

Reconstituted with 1 mL of Sterile Water for Injection at a concentration of 0.2 mg/mL, mitomycin is stable for one (1) hour at room temperature.

3 DOSAGE FORMS AND STRENGTHS

Mitosol® is a sterile lyophilized mixture of mitomycin and mannitol, which, when reconstituted with Sterile Water for Injection, provides a solution for application in glaucoma filtration surgery. Mitosol® is supplied in vials containing 0.2 mg of mitomycin. Each vial also contains mannitol 0.4 mg, at a 1:2 ratio of mitomycin to mannitol. Each mL of reconstituted solution contains 0.2 mg mitomycin and has a pH between 5.0 and 8.0.

4 CONTRAINDICATIONS

4.1 Hypersensitivity

Mitosol® is contraindicated in patients that have demonstrated a hypersensitivity to mitomycin in the past.

5 WARNINGS AND PRECAUTIONS

5.1 Cell Death

Mitomycin is cytotoxic. Use of mitomycin in concentrations higher than 0.2 mg/mL or use for longer than 2 minutes may lead to unintended corneal and/or scleral damage including thinning or perforation. Direct contact with the corneal endothelium will result in cell death.

5.2 Hypotony

The use of mitomycin has been associated with an increased incidence of post-operative hypotony.

5.3 Cataract Formation

Use in phakic patients has been correlated to a higher incidence of lenticular change and cataract formation.

5.4 Embryo-Fetal Toxicity

Based on findings in animals and mechanism of action, Mitosol® can cause fetal harm when administered to a pregnant woman. In animal reproduction studies, parenteral administration of mitomycin resulted in teratogenicity [see Use in Specific Populations (8.1, 8.3) and Clinical Pharmacology (12.1)].

6 ADVERSE REACTIONS

The following clinically significant adverse reactions are described elsewhere in the labeling:

- Cell Death [see Warnings and Precautions (5.1)]
- Hypotony [see Warnings and Precautions (5.2)]
- Cataract Formation [see Warnings and Precautions (5.3)]

6.1 Ophthalmic Adverse Reactions

Because clinical trials are conducted under widely varying conditions, adverse reaction rates observed in the clinical trials of a drug cannot be directly compared to rates in the clinical trials of another drug and may not reflect the rates observed in practice. The most frequent adverse reactions to Mitosol® occur locally, as an extension of the pharmacological activity of the drug. These reactions include:

Blebitis: bleb ulceration, chronic bleb leak, encapsulated/cystic bleb, bleb-related infection, wound dehiscence, conjunctival necrosis, thin-walled bleb

Cornea: corneal endothelial damage, epithelial defect, anterior synechiae, superficial punctuate keratitis, Descemet's detachment, induced astigmatism

Endophthalmitis

Hypotony: choroidal reactions (choroidal detachment, choroidal effusion, serous choroidal detachment, suprachoroidal hemorrhage, hypotony maculopathy, presence of supraciliochoroidal fluid, hypoechogenic suprachoroidal effusion)

Inflammation: iritis, fibrin reaction

Lens: cataract development, cataract progression, capsule opacification, capsular constriction and/or capsulotomy rupture, posterior synechiae

Retina: retinal pigment epithelial tear, retinal detachment (serous and rhegatogenous)

Scleritis: wound dehiscence

Vascular: hyphema, central retinal vein occlusion, hemiretinal vein occlusion, retinal hemorrhage, vitreal hemorrhage and blood clot, subconjunctival hemorrhage, disk hemorrhage

Additional Reactions: macular edema, sclera thinning or ulceration, intraocular lens capture, disk swelling, malignant glaucoma, lacrimal drainage system obstruction, ciliary block, corneal vascularization, visual acuity decrease, cystic conjunctival degeneration, upper eyelid retraction, dislocated implants, severe loss of vision.

8 USE IN SPECIFIC POPULATIONS

8.1 Pregnancy

Risk Summary

Based on findings in animals and mechanism of action [see Clinical Pharmacology (12.1)], Mitosol® can cause fetal harm when administered to a pregnant woman. There are no available data on Mitosol® use in pregnant women to inform the drug-associated risk. In animal reproduction studies, parenteral administration of mitomycin resulted in teratogenicity (see Data). Advise pregnant women of the potential risk to a fetus.

The estimated background risk of major birth defects and miscarriage for the indicated population is unknown. In the U.S. general population, the estimated background risk of major birth defects and miscarriage in clinically recognized pregnancies is 2% - 4% and 15% - 20%, respectively.

Data

Animal Data

Parenteral administration of mitomycin in animal reproduction studies produced fetal malformations and embryofetal lethality.

8.2 Lactation

Risk Summary

There are no data on the presence of mitomycin in human milk, the effects on the breastfed child, or the effects on milk production. Because of the potential for serious adverse reactions in a breastfed child, advise women not to breastfeed during and for 1 week following administration of Mitosol®.

8.3 Females and Males of Reproductive Potential

Mitosol® can cause fetal harm when administered to pregnant women [see Use in Specific Populations (8.1)].

Pregnancy Testing

Verify pregnancy status in females of reproductive potential prior to using Mitosol®.

8.4 Pediatric Use

Safety and effectiveness in pediatric patients have not been established.

8.5 Geriatric Use

No overall differences in safety and effectiveness have been observed between elderly and younger patients.

11 DESCRIPTION

Mitomycin is an antibiotic isolated from the broth of Streptomyces verticillus Yingtanensis which has been shown to have antimetabolic activity.

Mitomycin is a blue-violet crystalline powder with the molecular formula of C15H18N4O5 and a molecular weight of 334.33. Its chemical name is 7-amino-9α-methoxymitosane and it has the following structural formula:

Mitosol® is a sterile lyophilized mixture of mitomycin and mannitol, which, when reconstituted with Sterile Water for Injection, provides a solution for application in glaucoma filtration surgery. Mitosol® is supplied in vials containing 0.2 mg of mitomycin. Each vial also contains mannitol 0.4 mg, at a 1:2 ratio of mitomycin to mannitol. Each mL of reconstituted solution contains 0.2 mg mitomycin and has a pH between 5.0 and 8.0.

12 CLINICAL PHARMACOLOGY

12.1 Mechanism of Action

Mitosol® inhibits the synthesis of deoxyribonucleic acid (DNA). The guanine and cytosine content correlates with the degree of mitomycin-induced cross-linking. Cellular RNA and protein synthesis may also be suppressed.

12.3 Pharmacokinetics

Absorption

The systemic exposure of mitomycin following ocular administration of Mitosol® in humans is unknown. Based on a comparison of the proposed dose of up to 0.2 mg to intravenous (IV) doses of mitomycin used clinically for treatment of oncologic indications (up to 20 mg/m^2), systemic concentrations in humans upon ocular administration are expected to be multiple orders of magnitude lower than those achieved by IV administration.

Elimination

Metabolism

In humans, mitomycin is cleared from ophthalmic tissue after intraoperative topical application and irrigation, as metabolism occurs in other affected tissues. Systemic clearance is affected primarily by metabolism in the liver. The rate of clearance is inversely proportional to the maximal serum concentration because of saturation of the degradative pathways.

Excretion

Approximately 10% of an injectable dose of mitomycin is excreted unchanged in the urine. Since metabolic pathways are saturated at relatively low doses, the percent of a dose excreted in urine increases.

13 NONCLINICAL TOXICOLOGY

13.1 Carcinogenesis, Mutagenesis, Impairment of Fertility

Adequate long-term studies in animals to evaluate carcinogenic potential have not been conducted with Mitosol®. Intravenous administration of mitomycin has been found to be carcinogenic in rats and mice. At doses approximating the recommended clinical injectable dose in humans, mitomycin produces a greater than 100 percent increase in tumor incidence in male Sprague-Dawley rats, and a greater than 50 percent increase in tumor incidence in female Swiss mice.

The effect of Mitosol® on fertility is unknown.

14 CLINICAL STUDIES

In placebo-controlled studies reported in the medical literature, mitomycin reduced intraocular pressure (IOP) by 3 mmHg in patients with open-angle glaucoma when used as an adjunct to ab externo glaucoma surgery by Month 12.

In studies with a historical control reported in the medical literature, mitomycin reduced intraocular pressure (IOP) by 5 mmHg in patients with open-angle glaucoma when used as an adjunct to ab externo glaucoma surgery by Month 12.

16 HOW SUPPLIED/STORAGE AND HANDLING

16.1 How Supplied

Mitosol® (mitomycin for solution) is available in a kit containing:

One Vial containing 0.2 mg mitomycin

One 1 mL syringe (Sterile Water For Injection) with Safety Connector

One Plunger Rod

One Vial Adapter with Spike

One 1 mL TB Syringe, Luer Lock

One Sponge Container

Six 3 mm Absorbent Sponges

Six 6 mm Absorbent Sponges

Six Half Moon Sponges

One Instrument Wedge Sponge

One Protective Foam Pouch

One Chemotherapy Waste Bag

One Label, MMC (mitomycin)

Three kits are supplied in each carton (NDC 49771-002-03).

16.2 Storage and Handling

Storage

Store kits at 20°C to 25°C (68°F to 77°F). Avoid excessive heat. Protect from light.

Handling Procedures

Mitosol® is a cytotoxic drug. Procedures for Proper Handling and Disposal of anti-cancer drugs should be followed. Appropriate containment and disposal devices are included within the Mitosol® (mitomycin for solution) Kit for Ophthalmic Use.

17 PATIENT COUNSELING INFORMATION

- Instruct patients to discuss with their physician if they are pregnant or if they might become pregnant [see Use in Specific Populations (8.1)].
- Instruct patients to discuss with their physician if they have demonstrated a hypersensitivity to mitomycin in the past [see Contraindications (4.1)].
- Nursing mothers should be advised that it is not known if Mitosol® is excreted in human milk. Because of the potential for serious adverse reactions in a breastfed child, advise women not to breastfeed during and for 1 week following administration of Mitosol® [see Use in Specific Populations (8.2)].
- Patients should be advised of the toxicity of Mitosol® and potential complications.

Manufactured for:
Mobius Therapeutics, LLC
1000 Executive Parkway
Suite 224
St. Louis, MO 63141

INSTRUCTIONS FOR USE

Mitosol®
(mitomycin for solution)
0.2 mg/vial
Kit for Ophthalmic Use

Read INSTRUCTIONS FOR USE Before Proceeding

Instructions for Use

A. Outer Pack
(Figure A)

One Sterile Chemotherapy Waste Bag

One Instructions for Use

One Package Insert

One Inner Tray

Two Patient Chart Labels

The Outer Pack is to be handled, opened, and its STERILE contents dispensed by the non-sterile circulating nurse.

B. STERILE Inner Tray
(Figure B)

One Vial Containing 0.2 mg mitomycin (inside protective foam pouch)

One 1 mL Syringe (Sterile Water for Injection) with Safety Connector

One Plunger Rod

One Vial Adaptor with Spike (inside protective foam pouch)

One 1 mL TB Syringe, Luer Lock

One Sponge Container Containing:

• Six 3 mm Absorbent Sponges

• Six 6 mm Absorbent Sponges

• Six Half Moon Sponges

• One Instrument Wedge Sponge

One Label, MMC (mitomycin)

The Sterile Inner Tray is to be handled, opened, and its contents assembled and dispensed by the sterile scrub technician.

This tray and its contents are STERILE.

1. Getting Started

Non-Sterile Circulating Nurse:

Open outer pack. Affect sterile transfer of ALL contents to the sterile field.

Sterile Surgical Technician:

Open sterile inner tray.

2. Reconstituting Mitosol®

a. Remove vial and vial adapter from blue foam pouch.

b. Screw white plunger rod to rubber plunger of pre‑filled syringe. (Fig. 1)

c. Press firmly and screw the blue end of the vial adapter into the blue end of the syringe connector. (Fig. 2)

NOTE: Do not force plunger. Syringe will not operate if vial adapter and syringe connector are not properly connected. Forcing plunger may result in syringe leakage and Mitosol® exposure.

d. Stand vial upright on a sturdy, flat surface and push on the vial lid until seated and secure. (Fig. 3)

e. Inject entire contents of sterile water (1 ml) into vial. (Fig. 4) Do not force syringe plunger. See note at step 2.

f. IMPORTANT: INVERT VIAL REPEATEDLY to saturate ALL drug product, including that adhering to stopper, then shake until complete reconstitution of Mitosol®. If product does not dissolve immediately, allow to stand at room temperature until the product has dissolved into solution.

3. Preparing sponges

a. Invert vial and syringe and draw full volume of medication into syringe. (Fig. 5)

b. Remove all sponges from sponge tray.

c. Return to sponge tray only those sponges to be saturated with Mitosol®.

d. Unscrew the syringe with safety connector from vial and vial adapter. (Fig. 6) Note: DO NOT remove safety connector from syringe.

e. Place vial and vial adaptor in chemotherapy waste disposal bag (yellow bag), and set bag aside, within sterile field, for additional use.

f. Take sponge container from sterile inner tray.

g. Screw both syringes into sponge container; the TB syringe to one end, the syringe with reconstituted Mitosol® to the other.

h. Mitosol® must be used within 1 hour of reconstitution:

• Inject medication into sponge container, saturating sponges. Reconstituted Mitosol® should remain undisturbed in sponge container for 60 seconds. (Fig. 7) Do not force syringe plunger. See note at step 2.

• If any excess fluid remains, withdraw plunger of TB syringe, drawing excess fluid/air into syringe.

4. Using Mitosol®

a. With both syringes connected, the TB syringe to one end, the pre-filled syringe to the other, open sponge container, offering contents to surgeon for placement on surgical site. (Fig. 8)

b. Apply saturated sponges to surgical site for two minutes. Remove sponges from eye and copiously irrigate surgical site.

c. As used sponges are removed from surgical site, accept used sponges back into sponge container for disposal. Close container lid.

d. With syringes still connected to sponge container, remove entire assembly from surgical field in chemotherapy waste disposal bag.

DISPOSE OF CHEMOTHERAPY WASTE BAG AND ITS CONTENTS AS CHEMOTHERAPY WASTE

US Patents #7,806,265, #8,186,511, #D685,962, #D685,963, #9,205,075, #9,539,241 and #9,649,428; other international patents issued and pending.

A4807998-2
Rev. 07/20

PRINCIPAL DISPLAY PANEL - VIAL LABEL

Vial Label

NDC 49771-002-02

Mitosol®
(mitomycin for solution)

0.2 mg/vial

Lyophilized Mitomycin for
reconstitution
For ophthalmic use
Protect from light.
Single Use Vial
Dose: See Package Insert.

Rx Only

Store at 20°-25°C (68°-77°F).

Manufactured for:
Mobius Therapeutics, LLC
1000 Executive Parkway
Suite 224
St. Louis, MO 63141

Manufactured by:
Intas Pharmaceuticals Ltd.
Ahmedabad-382 210, INDIA.

Mfg. Lic. No.: G/28/1026

10 9480 0 6029283 INL5021

PRINCIPAL DISPLAY PANEL - VIAL LABEL-New

Vial Label

NDC 49771-002-02

Mitosol®
(mitomycin for solution)

0.2 mg/vial

Lyophilized Mitomycin for
reconstitution
For ophthalmic use
Protect from light.
Single Use Vial
Dose: See Package Insert.

Rx Only

Store at 20°-25°C (68°-77°F).

Manufactured for:
Mobius Therapeutics, LLC
1000 Executive Parkway
Suite 224
St. Louis, MO 63141

Lot:
EXP Date
YYYY-MM-DD

PRINCIPAL DISPLAY PANEL - OUTER KIT PACKAGE

Outer Kit Package

Mitosol®
(mitomycin for solution)
0.2 mg/vial

Kit for Ophthalmic Use

Manufactured for:
Mobius Therapeutics, LLC
1000 Executive Parkway
Suite 224
St. Louis, MO 63141 USA
+1 314-615-6930
1-877-EYE-MITO (1-877-393-6486)

Rx ONLY

US Patents #7,806,265, #8,186,511, #D685,962,
#D685,963, #9,205,075, #9,539,241 and #9,649,428;
other international patents issued and pending.

©2019 Mobius Therapeutics, LLC

mobius
therapeutics™

A1426418-1
Rev. 8/19

NDC #49771-002-01
Re-Order #MOB.2

Each Mitosol® Kit Contains:
One Chemotherapy Waste Bag
One Instructions for Use
One Package Insert
One Inner Tray
Two Patient Chart Labels

Inner Tray Contains:
One Vial Containing 0.2 mg mitomycin
(inside protective foam pouch)
One 1 mL Syringe (Sterile Water for Injection)
with Safety Connector
One Plunger Rod
One Vial Adaptor with Spike (inside protective foam pouch)
One 1 mL TB Syringe, Luer Lock
One Sponge Container Containing:
Six 3 mm Absorbent Sponges
Six 6 mm Absorbent Sponges
Six Half Moon Sponges
One Instrument Wedge Sponge
One Label, MMC

Contents STERILE in unopened undamaged package.

Storage: Store kits at 20° - 25° C (68° - 77° F). Protect from light.

HD CAUTION: HAZARDOUS DRUG
OBSERVE SPECIAL HANDLING, ADMINISTRATION
AND DISPOSAL REQUIREMENTS